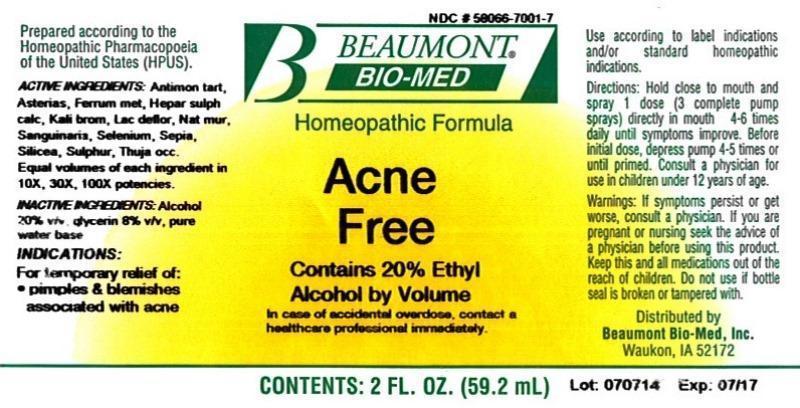 DRUG LABEL: Acne Free
NDC: 58066-7001 | Form: LIQUID
Manufacturer: Beaumont Bio Med
Category: homeopathic | Type: HUMAN OTC DRUG LABEL
Date: 20150108

ACTIVE INGREDIENTS: ANTIMONY POTASSIUM TARTRATE 10 [hp_X]/59.2 mL; ASTERIAS RUBENS 10 [hp_X]/59.2 mL; IRON 10 [hp_X]/59.2 mL; CALCIUM SULFIDE 10 [hp_X]/59.2 mL; POTASSIUM BROMIDE 10 [hp_X]/59.2 mL; SKIM MILK 10 [hp_X]/59.2 mL; SODIUM CHLORIDE 10 [hp_X]/59.2 mL; SANGUINARIA CANADENSIS ROOT 10 [hp_X]/59.2 mL; SELENIUM 10 [hp_X]/59.2 mL; SEPIA OFFICINALIS JUICE 10 [hp_X]/59.2 mL; SILICON DIOXIDE 10 [hp_X]/59.2 mL; SULFUR 10 [hp_X]/59.2 mL; THUJA OCCIDENTALIS LEAFY TWIG 10 [hp_X]/59.2 mL
INACTIVE INGREDIENTS: ALCOHOL; GLYCERIN; WATER

Acne Free

ACTIVE INGREDIENT

HPUS active ingredients: Antimonium tartaricum, Asterias rubens, Ferrum metallicum, Hepar sulphuris calcareum, Kali bromatum, Lac defloratum, Natrum muriaticum, Sanguinaria canadensis, Selenium metallicum, Sepia, Silicea, Sulphur, Thuja occidentalis. Equal volumes of each ingredient in 10X, 30X, 100X potencies.

INACTIVE INGREDIENT

Inactive Ingredients: Alcohol @ (20% v/v), Glycerin @ (8% v/v), in a pure water base.

INDICATIONS AND USAGE

Indications: For temporary relief of: •pimples & blemishes associated with acne.

Directions:

- Hold close to mouth and spray 1 dose (3 complete pump sprays) directly in mouth 4-6 times daily until symptoms improve.
- Before initial dose, depress pump 4-5 times or until primed.
- Consult a physician for use in children under 12 years of age.

Use according to label indications and/or standard homeopathic indications.

WARNINGS

Warnings: If symptoms persist or get worse, consult a physician. If you are pregnant or nursing seek the advice of a physician before using this product. Keep this and all medications out of the reach of children. Do not use if bottle seal is broken or tampered with.

- Keep out of reach of children.

PURPOSE

For temporary relief of:

- pimples & blemishes associated with acne